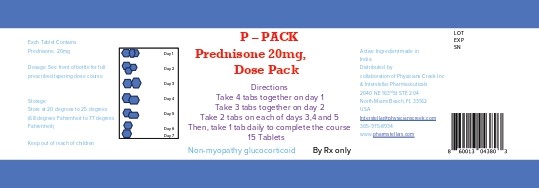 DRUG LABEL: P- PACK PREDNISONE 20MG, 7- DAY TAPERING DOSE PACK
NDC: 85000-0012 | Form: TABLET
Manufacturer: INTERSTELLAR PHARMACEUTICALS INC.
Category: prescription | Type: HUMAN PRESCRIPTION DRUG LABEL
Date: 20250211

ACTIVE INGREDIENTS: PREDNISONE 20 mg/1 1
INACTIVE INGREDIENTS: LACTOSE MONOHYDRATE; SILICON DIOXIDE

P- PACK PREDNISONE 20MG, 7- DAY TAPERING DOSE PACK

PATIENT INFORMATION

Take 4 tabs together on day 1
Take 3 tabs together on day 2
Take 2 tabs on each of days 3,4 and 5
Then, take 1 tab daily to complete the course
15 Table t s

P-Pack Pednisone

P-Pack Prednisone